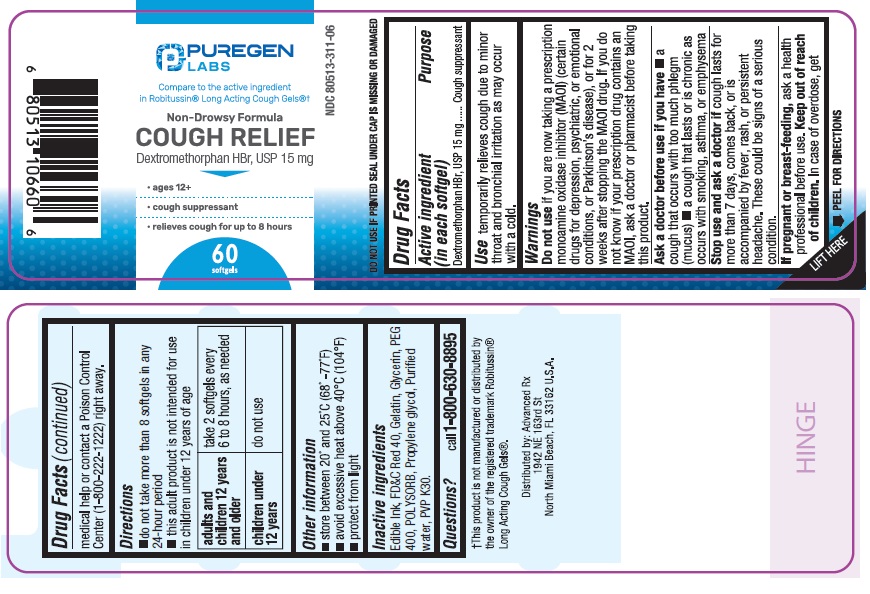 DRUG LABEL: Cough Relief
NDC: 80513-311 | Form: CAPSULE, LIQUID FILLED
Manufacturer: Advanced Rx LLC
Category: otc | Type: HUMAN OTC DRUG LABEL
Date: 20250101

ACTIVE INGREDIENTS: DEXTROMETHORPHAN HYDROBROMIDE 15 mg/1 1
INACTIVE INGREDIENTS: FD&C RED NO. 40; GELATIN; GLYCERIN; POLYETHYLENE GLYCOL 400; PROPYLENE GLYCOL; POVIDONE K30; WATER

Cough Relief

Active Ingredient (in each tablet)

Dextromethorphan HBr, USP 15 mg

Purpose

Cough suppressant

Uses

temporarily relieves cough due to minor throat and bronchial irritation as may occur with a cold.

Warnings

Do not useif you are now taking a prescription monoamine oxidase inhibitor (MAOI) (certain drugs for depression, psychiatric, or emotional conditions, or Parkinson's disease), or for 2 weeks after stopping the MAOI drug. If you do not know if your prescription drug contains an MAOI, ask a doctor or pharmacist before taking this product.

Ask a doctor before use if you have

• a cough that occurs with too much phlegm (mucus)

• a cough that lasts or is chronic as occurs with smoking, asthma, or emphysema

Stop use and ask a doctor if

cough lasts for more than 7 days, comes back, or is accompanied by fever, rash, or persistent headache. These could be signs of a serious condition.

If pregnant or breast-feeding,

ask a health professional before use

Keep out of reach of children.

In case of overdose, get medical help or contact a Poison Control Center (1-800-222-1222) right away.

Directions

- do not take more than 8 softgels in any 24-hour period
- this adult product is not intended for use in children under 12 years of age

adults and children 12 years and older | take 2 softgels every 6 to 8 hours, as needed
children under 12 years | do not use

Other information

• store between 20° and 25°C (68°–77°F)

• avoid excessive heat above 40°C (104°F)

• protect from light

• DO NOT USE IF PRINTED SEAL UNDER CAP IS MISSING OR DAMAGED

Inactive ingredients

Edible Ink, FD&C Red No. 40, Gelatin, Glycerin, Polyethylene Glycol 400, POLYSORB, Propylene Glycol, Purified Water, Povidone K30.

Questions?

Call 1-800-630-8895

Distributed by:

Advanced Rx LLC

1942 NE 163rd St

North Miami Beach,

FL 33162 U.S.A.

PACKAGE LABEL

NDC 80513-311-06

Cough Relief